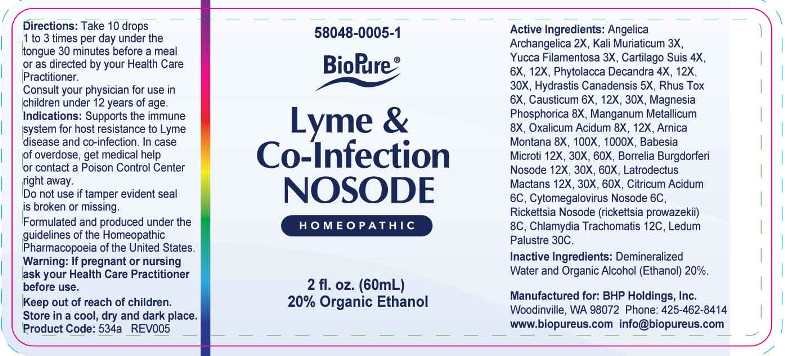 DRUG LABEL: Lyme and Co-Infection Nosode
NDC: 58048-0005 | Form: LIQUID
Manufacturer: Bhp Holdings, Inc.
Category: homeopathic | Type: HUMAN OTC DRUG LABEL
Date: 20230601

ACTIVE INGREDIENTS: ANGELICA ARCHANGELICA ROOT 2 [hp_X]/1 mL; POTASSIUM CHLORIDE 3 [hp_X]/1 mL; YUCCA FILAMENTOSA 3 [hp_X]/1 mL; SUS SCROFA CARTILAGE 4 [hp_X]/1 mL; PHYTOLACCA AMERICANA ROOT 4 [hp_X]/1 mL; GOLDENSEAL 5 [hp_X]/1 mL; TOXICODENDRON PUBESCENS LEAF 6 [hp_X]/1 mL; CAUSTICUM 6 [hp_X]/1 mL; MAGNESIUM PHOSPHATE, DIBASIC TRIHYDRATE 8 [hp_X]/1 mL; MANGANESE 8 [hp_X]/1 mL; OXALIC ACID 8 [hp_X]/1 mL; ARNICA MONTANA 8 [hp_X]/1 mL; BABESIA MICROTI 12 [hp_X]/1 mL; BORRELIA BURGDORFERI 12 [hp_X]/1 mL; LATRODECTUS MACTANS 12 [hp_X]/1 mL; ANHYDROUS CITRIC ACID 6 [hp_C]/1 mL; HUMAN HERPESVIRUS 5 6 [hp_C]/1 mL; RICKETTSIA PROWAZEKII 8 [hp_C]/1 mL; CHLAMYDIA TRACHOMATIS 12 [hp_C]/1 mL; LEDUM PALUSTRE TWIG 30 [hp_C]/1 mL
INACTIVE INGREDIENTS: WATER; ALCOHOL

Drug Facts:

ACTIVE INGREDIENTS:

Angelica Archangelica 2X, Kali Muriaticum 3X, Yucca Filamentosa 3X, Cartilago Suis 4X, 6X, 12X, Phytolacca Decandra 4X, 12X, 30X, Hydrastis Canadensis 5X, Rhus Tox 6X, Causticum 6X, 12X, 30X, Magnesia Phosphorica 8X, Manganum Metallicum 8X, Oxalicum Acidum 8X, 12X, Arnica Montana 8X, 100X, 1000X, Babesia Microti 12X, 30X, 60X, Borrelia Burgdorferi Nosode 12X, 30X, 60X, Latrodectus Mactans 12X, 30X, 60X, Citricum Acidum 6C, Cytomegalovirus Nosode 6C, Rickettsia Nosode (Rickettsia prowazekii) 8C, Chlamydia Trachomatis 12C, Ledum Palustre 30C.

INDICATIONS:

Supports the immune system for host resistance to Lyme disease and co-infections.

WARNINGS:

If pregnant or nursing ask your health Care Practitioner before use.

Keep out of reach of children. In case of overdose, get medical help or contact a Poison Control Center right away.

Do not use if tamper evident seal is broken or missing.

Store in a cool, dry and dark place.

Keep out of reach of children. In case of overdose, get medical help or contact a Poison Control Center right away.

DIRECTIONS:

Take 10 drops 1 to 3 times per day under the tongue 30 minutes before meal or as directed by a Health Care Practitioner.
Consult your physician for use in children under 12 years of age.

INDICATIONS:

Supports the immune system for host resistance to Lyme disease and co-infections.

INACTIVE INGREDIENTS:

Demineralized Water and Organic Alcohol (Ethanol) 20%.

QUESTIONS:

Manufactured for: BHP Holdings, Inc.

Woodinville, WA 98072 Phone: 425-462-8414

www.biopureus.com info@biopureus.com

Formulated and produced under the guidelines of the Homeopathic Pharmacopoeia of the United States.

PACKAGE LABEL DISPLAY:

58048-0005-1

BioPure

Lyme & Co-Infection

NOSODE

HOMEOPATHIC

2 fl.oz (60mL)